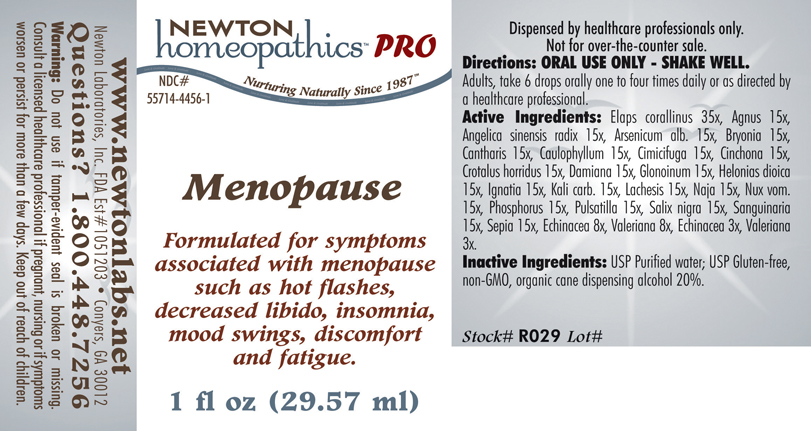 DRUG LABEL: Menopause 
NDC: 55714-4456 | Form: LIQUID
Manufacturer: Newton Laboratories, Inc.
Category: homeopathic | Type: HUMAN PRESCRIPTION DRUG LABEL
Date: 20110601

ACTIVE INGREDIENTS: Micrurus Corallinus Venom 35 [hp_X]/1 mL; Chaste Tree 15 [hp_X]/1 mL; Angelica Sinensis Root 15 [hp_X]/1 mL; Arsenic Trioxide 15 [hp_X]/1 mL; Bryonia Alba Root 15 [hp_X]/1 mL; Lytta Vesicatoria 15 [hp_X]/1 mL; Caulophyllum Thalictroides Root 15 [hp_X]/1 mL; Black Cohosh 15 [hp_X]/1 mL; Cinchona Officinalis Bark 15 [hp_X]/1 mL; Crotalus Horridus Horridus Venom 15 [hp_X]/1 mL; Turnera Diffusa Leafy Twig 15 [hp_X]/1 mL; Nitroglycerin 15 [hp_X]/1 mL; Chamaelirium Luteum Root 15 [hp_X]/1 mL; Strychnos Ignatii Seed 15 [hp_X]/1 mL; Potassium Carbonate 15 [hp_X]/1 mL; Lachesis Muta Venom 15 [hp_X]/1 mL; Naja Naja Venom 15 [hp_X]/1 mL; Strychnos Nux-vomica Seed 15 [hp_X]/1 mL; Phosphorus 15 [hp_X]/1 mL; Pulsatilla Vulgaris 15 [hp_X]/1 mL; Salix Nigra Bark 15 [hp_X]/1 mL; Sanguinaria Canadensis Root 15 [hp_X]/1 mL; Sepia Officinalis Juice 15 [hp_X]/1 mL; Echinacea, Unspecified 8 [hp_X]/1 mL; Valerian 8 [hp_X]/1 mL
INACTIVE INGREDIENTS: Alcohol

Menopause

INDICATIONS & USAGE SECTION

Menopause Formulated for symptoms associated with menopause such as hot flashes, decreased libido, insomnia, mood swings, discomfort and fatigue.

DOSAGE & ADMINISTRATION SECTION

Directions: ORAL USE ONLY - SHAKE WELL. Adults, take 6 drops orally one to four times daily or as directed by a healthcare professional.

ACTIVE INGREDIENT SECTION

Elaps corallinus 35x, Agnus 15x, Angelica sinensis radix 15x, Arsenicum alb. 15x, Bryonia 15x, Cantharis 15x, Caulophyllum 15x, Cimicifuga 15x, Cinchona 15x, Crotalus horridus 15x, Damiana 15x, Glonoinum 15x, Helonias dioica 15x, Ignatia 15x, Kali carb. 15x, Lachesis 15x, Naja 15x, Nux vom.15x, Phosphorus 15x, Pulsatilla 15x, Salix nigra 15x, Sanguinaria 15x, Sepia 15x, Echinacea 8x, Valeriana 8x, Echinacea 3x, Valeriana3x.

PURPOSE SECTION

Formulated for symptoms associated with menopause such as hot flashes, decreased libido, insomnia, mood swings, discomfort and fatigue.

INACTIVE INGREDIENT SECTION

Inactive Ingredients: USP Purified Water; USP Gluten-free, non-GMO, organic cane dispensing alcohol 20%.

QUESTIONS? SECTION

www.newtonlabs.net Newton Laboratories, Inc. FDA Est # 1051203 - Conyers, GA 30012
Questions? 1.800.448.7256

WARNINGS SECTION

Warning: Do not use if tamper - evident seal is broken or missing. Consult a licensed healthcare professional if pregnant, nursing or if symptoms worsen or persist for more than a few days. Keep out of reach of children.

PREGNANCY OR BREAST FEEDING SECTION

Consult a licensed healthcare professional if pregnant, nursing or if symptoms worsen or persist for more than a few days.

KEEP OUT OF REACH OF CHILDREN SECTION

Keep out of reach of children.